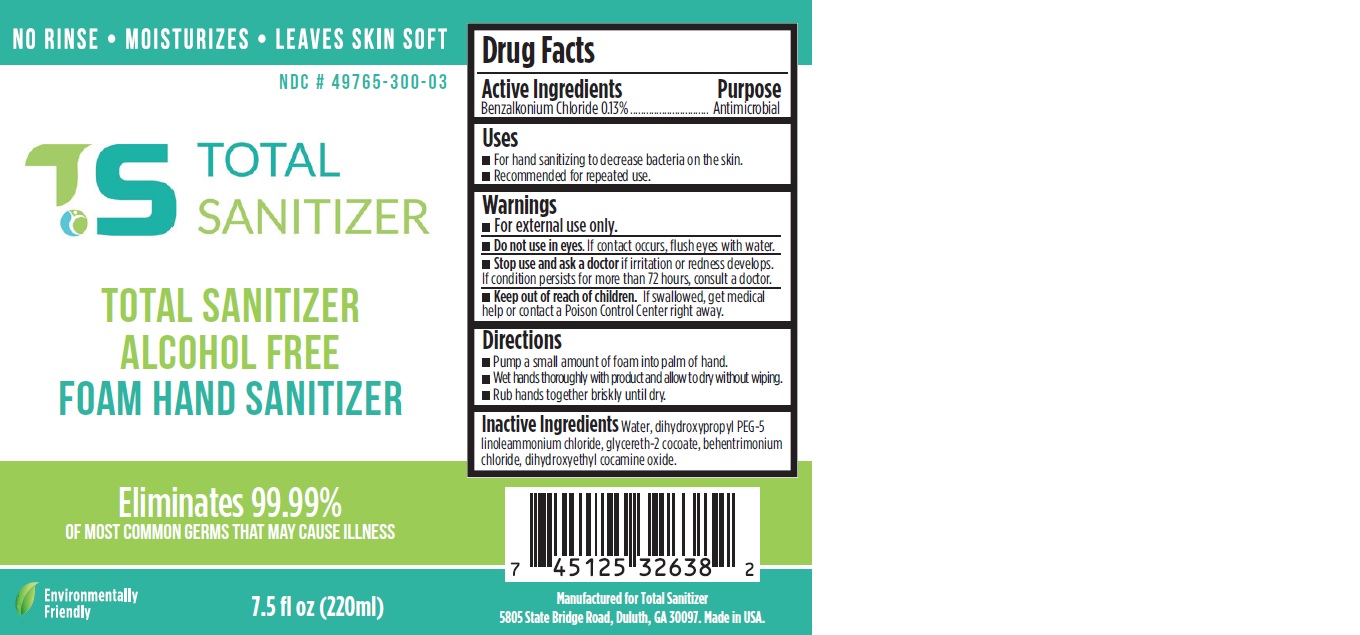 DRUG LABEL: Total Sanitizer Alcohol Free Foam Hand Sanitizer
NDC: 80463-001 | Form: LIQUID
Manufacturer: Total Sanitizer, LLC
Category: otc | Type: HUMAN OTC DRUG LABEL
Date: 20200910

ACTIVE INGREDIENTS: BENZALKONIUM CHLORIDE 1.3 mg/1 mL
INACTIVE INGREDIENTS: WATER; DIHYDROXYPROPYL PEG-5 LINOLEAMMONIUM CHLORIDE; GLYCERETH-2 COCOATE; BEHENTRIMONIUM CHLORIDE; DIHYDROXYETHYL COCAMINE OXIDE

Total Sanitizer Alcohol Free Foam Hand Sanitizer

Active Ingredients

Benzalkonium Chloride 0.13%

Purpose

Antimicrobial

Uses

- For hand sanitizing to decrease bacteria on the skin.
- Recommended for repeated use.

Warnings

- For external use only.

Do not use

- in eyes. If contact occurs, flush eyes with water.

Stop use and ask a doctor

- if irritation or redness develops. If condition persists for more than 72 hours, consult a doctor

Keep out of reach of children.

- If swallowed, get medical help or contact a Poison Control Center right away.

Directions

- Pump a small amount of foam into palm of hand.
- Wet hands thoroughly with product and allow to dry without wiping.
- Rub hands together briskly until dry.

Inactive Ingredients

Water, dihydroxypropyl PEG-5 linoleammonium chloride, glycereth-2 cocoate, behentrimonium chloride, dihydroxyethyl cocamine oxide.